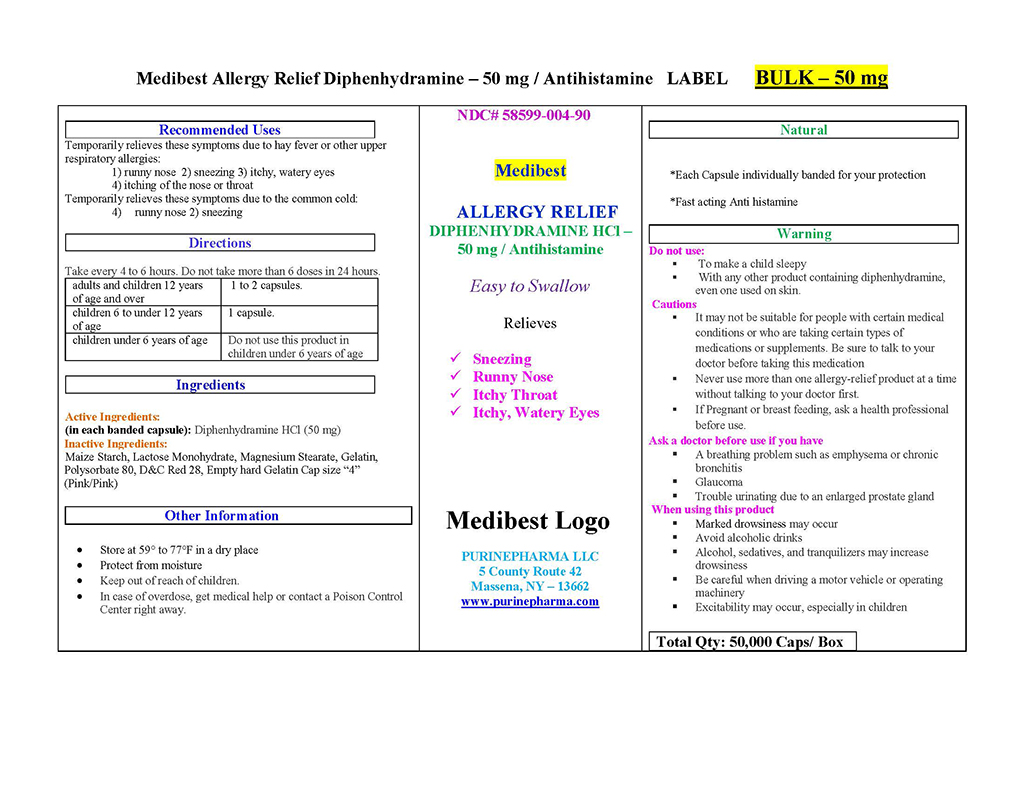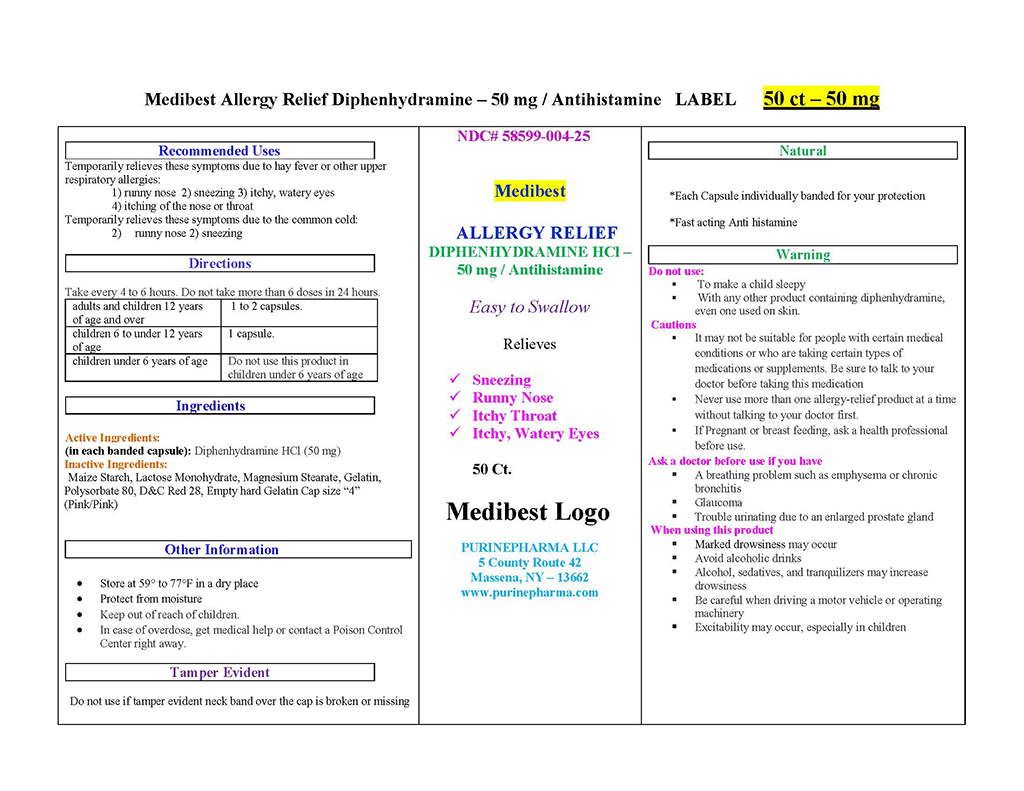 DRUG LABEL: DIPHENHYDRAMINE
NDC: 58599-004 | Form: CAPSULE
Manufacturer: PURINEPHARMA LLC
Category: otc | Type: HUMAN OTC DRUG LABEL
Date: 20140814

ACTIVE INGREDIENTS: DIPHENHYDRAMINE HYDROCHLORIDE 50 mg/1 1
INACTIVE INGREDIENTS: D&C RED NO. 28; GELATIN; LACTOSE MONOHYDRATE; MAGNESIUM STEARATE; STARCH, CORN; POLYSORBATE 80

DIPHENHYDRAMINE HCl CAPSULES

Active Ingredient (each banded capsule contains)

Diphenhydramine HCL 50 mg

Purpose

Antihistaminne

Uses

- temporarily relieves these symptoms due to hay fever or other upper respiratory allergies:
  - runny nose
  - sneezing
  - itchy, Watery eyes
  - itching of the nose or throat

WARNINGS

Ask a doctor before use if you have

- a breathing problem such as chronic bronchitis
- glaucoma
- trouble urinating due to an enlarged prostate gland

Do not use to make a child sleepy

Do not use with any other product containing diphenhydramine, even one used on skin

When using this product

- marked drowsiness may occur
- avoid alcoholic drinks
- alcohol, sedatives and tranquilizers may increase drowsiness
- be careful when driving a motor vehicle or operating machinery
- excitability may occur, especially in children

PREGNANCY OR BREAST FEEDING

If pregnant or breast-feeding, ask a health professional before use.

Keep out of reach of children, In case of overdose, get medical help or contact a Poison control center right away.

Directions:

- Take every 4 to 6 hours.
- Do not take more than 6 doses in any 24-hour period.

Adults and Children 12 years of age and over | 1 to 2 capsules
Children 6 to under 12 years of age | 1 capsule
Children under 6 years of age | Do not use

Other information

- Store between 15-30 degree Celsius (59-86 degree Fahrenheit)
- Protect from moisture

INACTIVE INGREDIENT

D&C red 28, gelatin, lactose monohydrate, magnesium stearate, maize starch, polysorbate tween 80, silica gel.

HOW SUPPLIED

Pack Size: 50 Capsules in a Bottle
Batch No.:
Mfg. Date:
Exp. Date:

OTHER SAFETY INFORMATION

TAMPER EVIDENT: DO NOT USE IF IMPRINTED SAFETY SEAL UNDER CAP IS BROKEN OR MISSING OR IF RED BAND AROUND CAPSULE IS BROKEN OR MISSING.

PACKAGE LABEL

NDC 58599-004-90
NDC 58599-004-25
NDC 58599-004-29
NDC 58599-004-35

Manufactured By: PURINEPHARMA LLC
5 County Route 42
Massena, NY – 13662
www.purinepharma.com